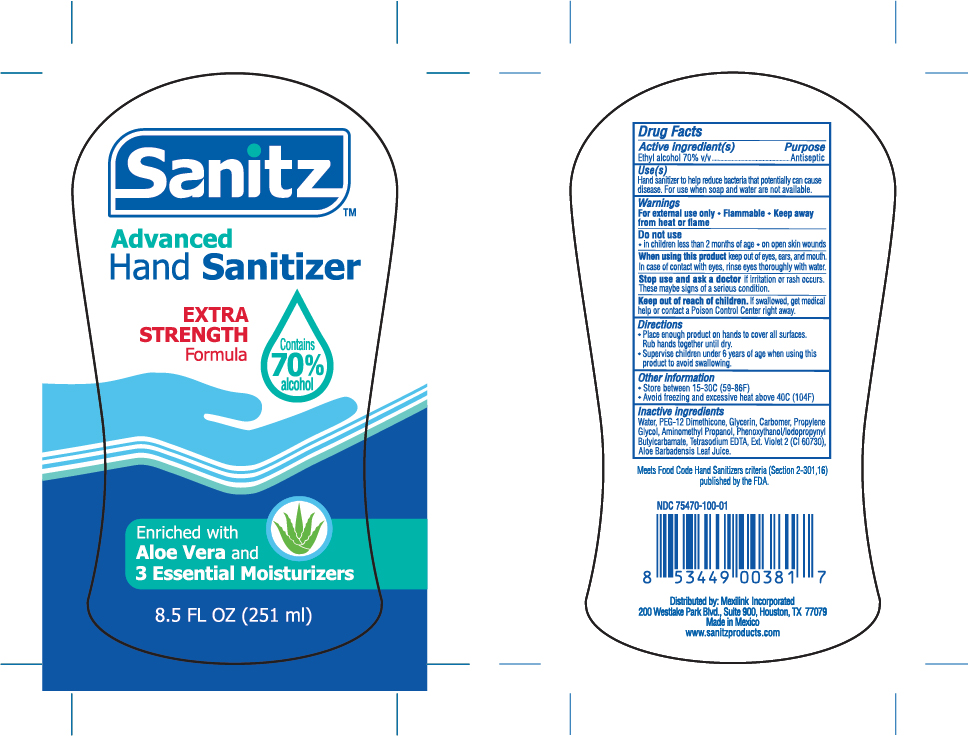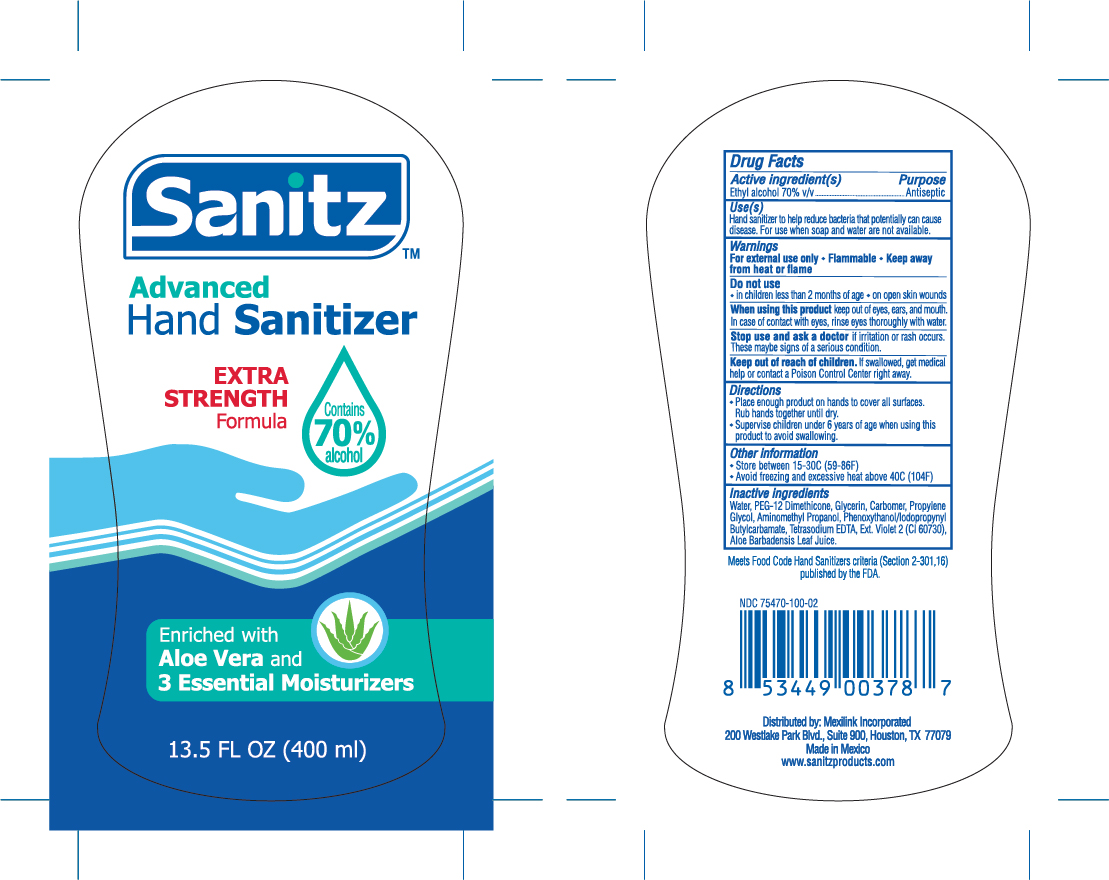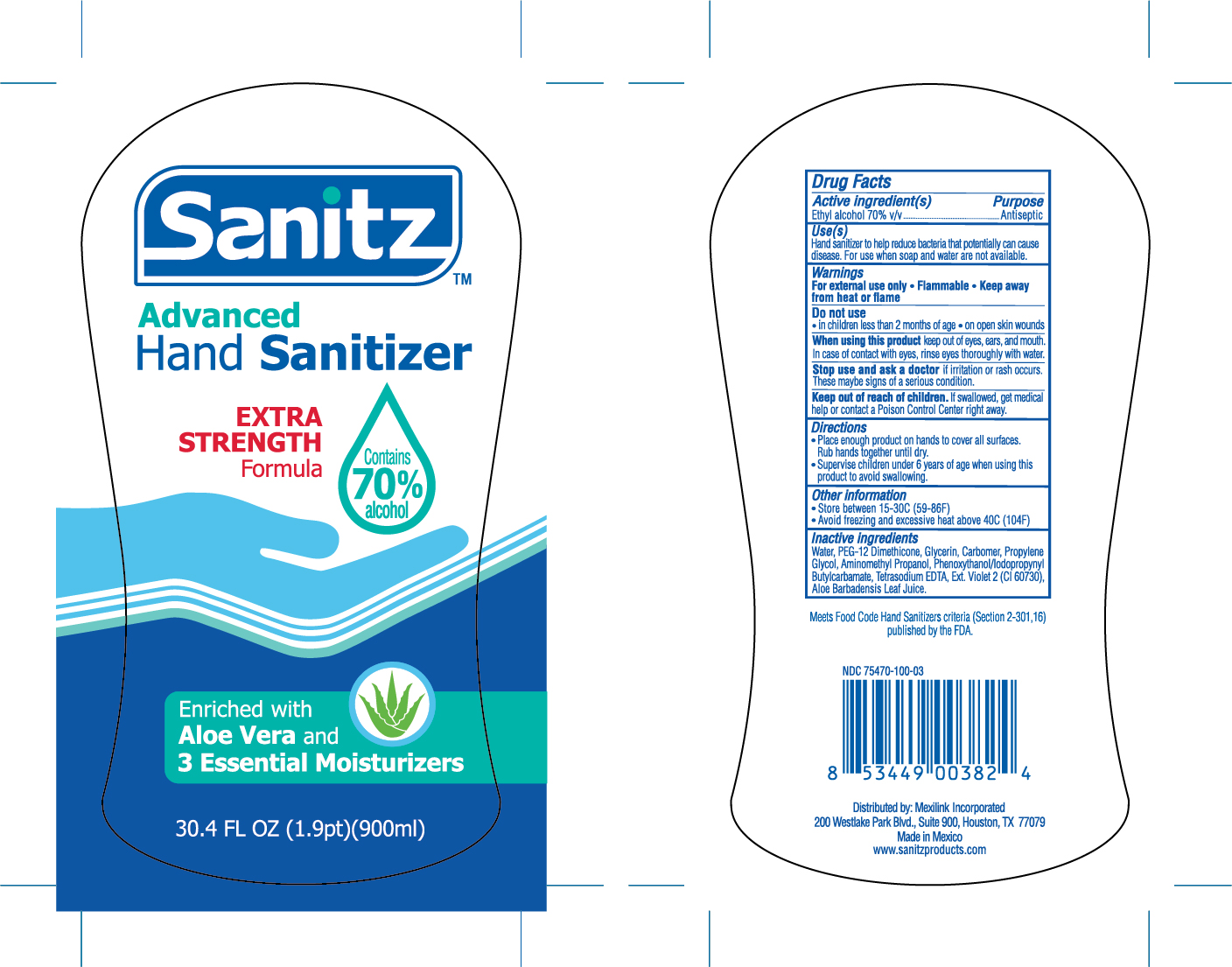 DRUG LABEL: Hand Sanitizer
NDC: 75470-110 | Form: LIQUID
Manufacturer: Tecnoglobal Ph7, S.a. De C.v.
Category: otc | Type: HUMAN OTC DRUG LABEL
Date: 20200825

ACTIVE INGREDIENTS: ALCOHOL 70 mL/100 mL
INACTIVE INGREDIENTS: CARBOMER 940; PHENOXYETHANOL; IODOPROPYNYL BUTYLCARBAMATE; EXT. D&C VIOLET NO. 2; GLYCERIN; WATER; PEG-12 DIMETHICONE; PROPYLENE GLYCOL; AMINOMETHYLPROPANOL; ALOE VERA LEAF; EDETATE SODIUM

Sanitz 75470-110

Active Ingredient(s)

Alcohol 70% v/v. Purpose: Antiseptic

Purpose

Antiseptic, Hand Sanitizer

Use

Hand Sanitizer to help reduce bacteria that potentially can cause disease. For use when soap and water are not available.

Warnings

For external use only. Flammable. Keep away from heat or flame

Do not use

- in children less than 2 months of age
- on open skin wounds

When using this product keep out of eyes, ears, and mouth. In case of contact with eyes, rinse eyes thoroughly with water.

Stop use and ask a doctor if irritation or rash occurs. These may be signs of a serious condition.

Keep out of reach of children. If swallowed, get medical help or contact a Poison Control Center right away.

Directions

- Place enough product on hands to cover all surfaces. Rub hands together until dry.
- Supervise children under 6 years of age when using this product to avoid swallowing.

Other information

- Store between 15-30C (59-86F)
- Avoid freezing and excessive heat above 40C (104F)

Inactive ingredients

Water, PEG-12 Dimethicone, Glycerin, Carbomer, Propylene Glycol, Aminomethyl Propanol, Phenoxyethanol, Iodoprpynyl Butylcarbamate, Tetrasodium EDTA, Ext. Violet 2, Aloe Barbadensis Leaf Juice

Package Label - Principal Display Panel

30mL NDC: 75470-110-05

60mL NDC: 75470-110-04

900mL NDC: 75470-110-03

400mL NDC: 75470-110-02

251mL NDC: 75470-110-01